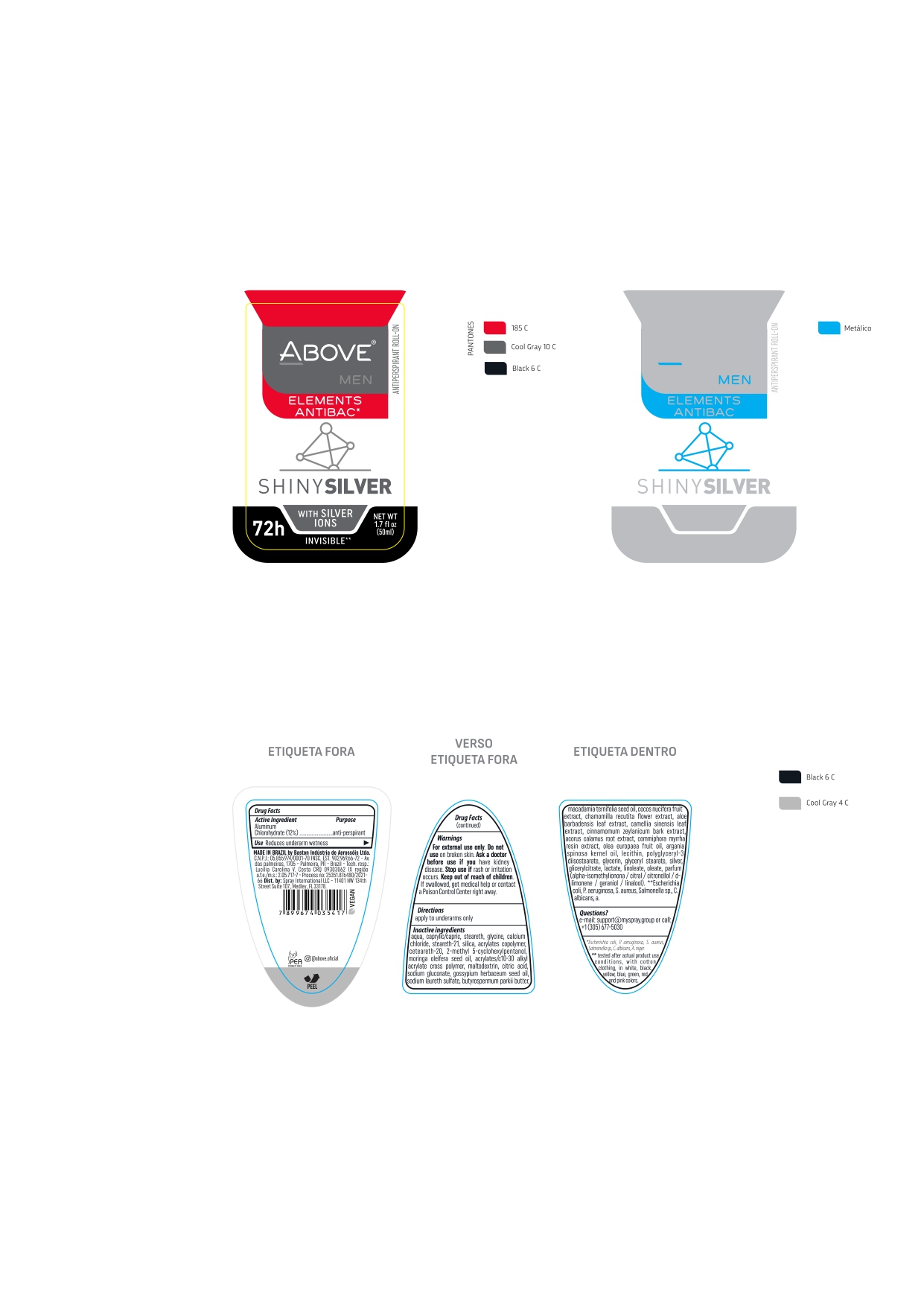 DRUG LABEL: ABOVE ELEMENTS ANTIBAC SHINYSILVER
NDC: 73306-1133 | Form: CREAM
Manufacturer: BASTON INDUSTRIA DE AEROSSOIS LTDA
Category: otc | Type: HUMAN OTC DRUG LABEL
Date: 20240709

ACTIVE INGREDIENTS: ALUMINUM CHLOROHYDRATE 12 mg/100 g
INACTIVE INGREDIENTS: MEDIUM-CHAIN TRIGLYCERIDES

ABOVE ELEMENTS ANTIBAC SHINYSILVER